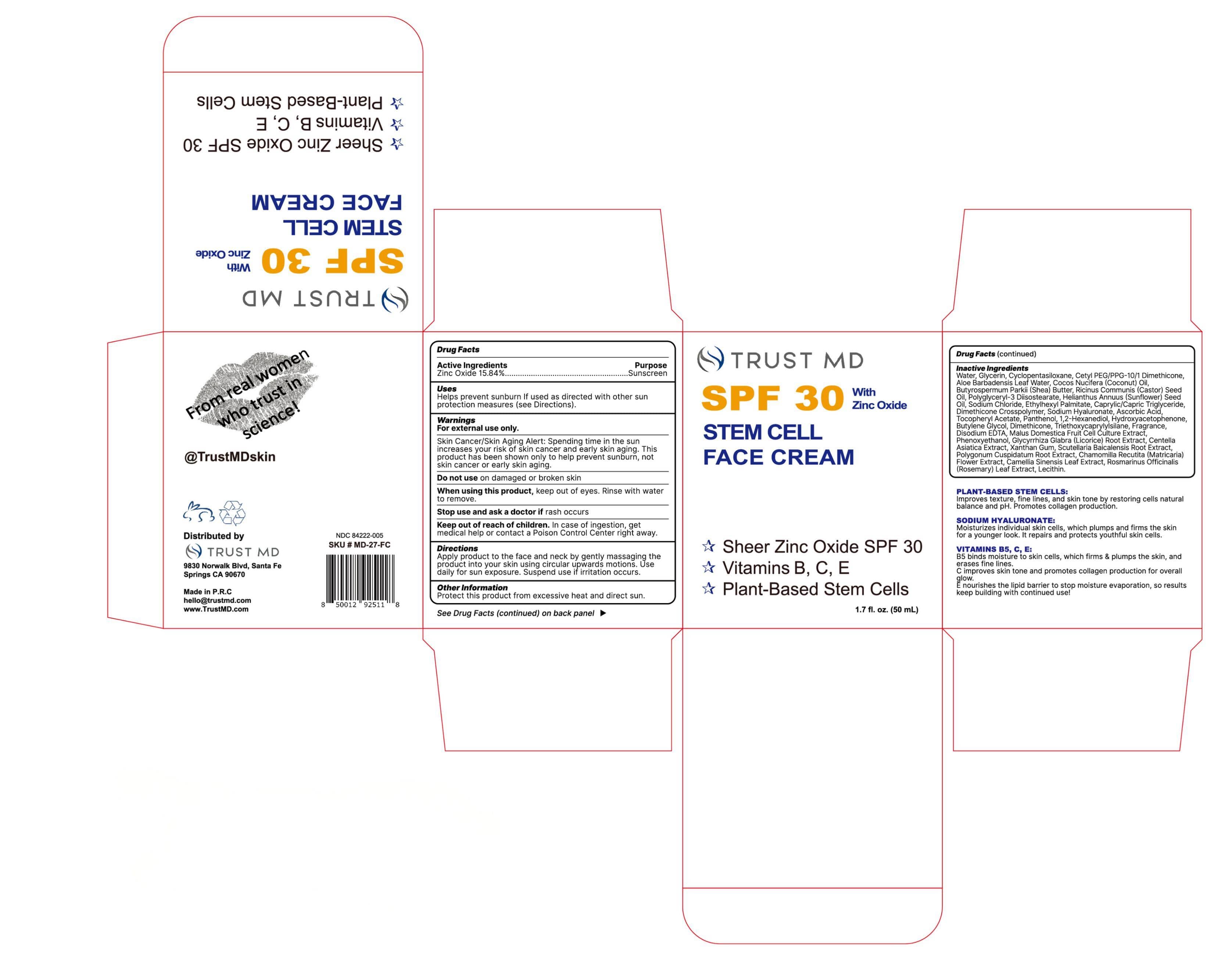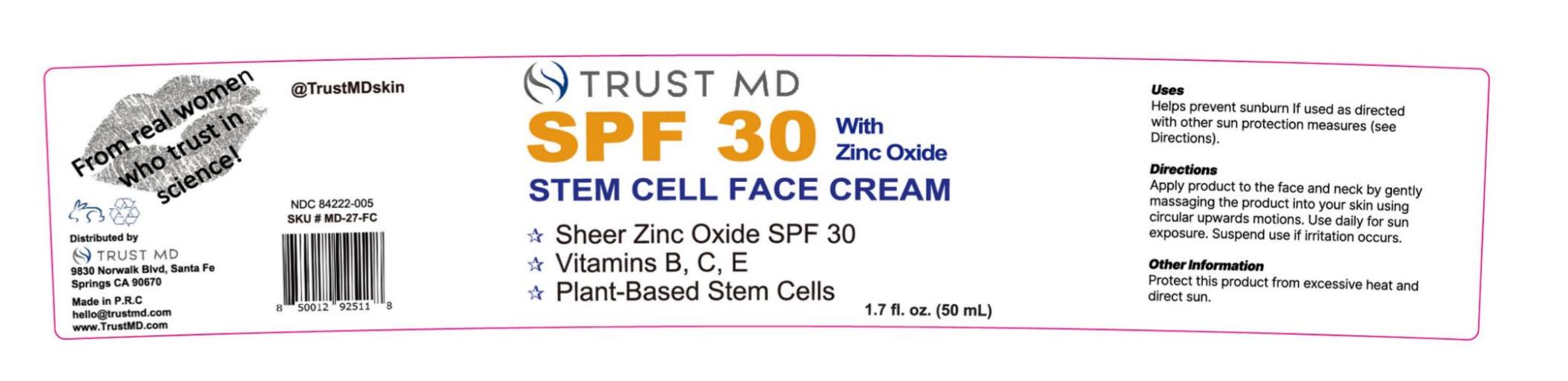 DRUG LABEL: TRUST MD SPF 30 FACECREAM
NDC: 84222-005 | Form: CREAM
Manufacturer: Foshan Miwei Cosmetics Co.,Ltd.
Category: otc | Type: HUMAN OTC DRUG LABEL
Date: 20250928

ACTIVE INGREDIENTS: ZINC OXIDE 15.84 g/100 mL
INACTIVE INGREDIENTS: PHENOXYETHANOL 0.0014 mL/100 mL; CYCLOPENTASILOXANE 3.48 mL/100 mL; PANTHENOL 0.5 mL/100 mL; GLYCYRRHIZA GLABRA (LICORICE) ROOT 0.00125 mL/100 mL; GREEN TEA LEAF 0.0005 mL/100 mL; ROSEMARY 0.00025 mL/100 mL; BUTYLENE GLYCOL 0.3 mL/100 mL; RICINUS COMMUNIS (CASTOR) SEED OIL 0.1 mL/100 mL; HELIANTHUS ANNUUS (SUNFLOWER) SEED OIL 2 mL/100 mL; SODIUM CHLORIDE 1 mL/100 mL; APPLE 0.009 mL/100 mL; XANTHAN GUM 0.001 mL/100 mL; SCUTELLARIA BAICALENSIS ROOT 0.00075 mL/100 mL; CHAMOMILE 0.00075 mL/100 mL; LECITHIN, SOYBEAN 0.00014 mL/100 mL; BUTYROSPERMUM PARKII (SHEA) BUTTER 0.1 mL/100 mL; SODIUM HYALURONATE 0.02 mL/100 mL; CETYL PEG/PPG-10/1 DIMETHICONE (HLB 5) 3.325 mL/100 mL; WATER 50.41281 mL/100 mL; ALOE VERA LEAF 0.2 mL/100 mL; COCOS NUCIFERA (COCONUT) OIL 0.1 mL/100 mL; POLYGLYCERYL-3 DIISOSTEARATE 2 mL/100 mL; ETHYLHEXYL PALMITATE 5 mL/100 mL; .ALPHA.-TOCOPHEROL ACETATE 0.5 mL/100 mL; 1,2-HEXANEDIOL 0.5 mL/100 mL; DIMETHICONE 0.175 mL/100 mL; REYNOUTRIA JAPONICA ROOT 0.00075 mL/100 mL; FRAGRANCE 13576 0.1 mL/100 mL; CAPRYLIC/CAPRIC TRIGLYCERIDE 5 mL/100 mL; EDETATE DISODIUM 0.05 mL/100 mL; DIMETHICONE CROSSPOLYMER 0.52 mL/100 mL; TRIETHOXYCAPRYLYLSILANE 0.16 mL/100 mL; ASCORBIC ACID 0.1 mL/100 mL; CENTELLA ASIATICA TRITERPENOIDS 0.001 mL/100 mL; GLYCERIN 8.0004 mL/100 mL; HYDROXYACETOPHENONE 0.5 mL/100 mL

TRUST MD SPF 30 With Zinc Oxide STEM CELL FACE CREAM

ACTIVE INGREDIENT

Zinc Oxide 15.84%

PURPOSE

Sunscreen

WARNINGS

For external use only.
Skin Cancer/Skin Aging Alert: Spending time in the sun
increases your risk of skin cancer and early skin aging.This
product hás been shown only to help prevent sunburn,not
skin cancer or early skin aging.
Do not use on damaged or broken skin
When using this product, keep out of eyes. Rinse with water
to remove.
Stop use and ask a doctor if rash occurs
Keep out of reach of children. In case of ingestion, get
medical help or contact a Poison Control Center right away.

When using this product, keep out of eyes. Rinse with water to remove

Do not use on damaged or broken skin

STOP USE

Stop using and ask a doctor if a rash occurs

Keep out of reach of children. In case of ingestion, get medical help or contact a Poison Control Center right away.

DOSAGE AND ADMINISTRATION

Apply product to the face and neck by gently massaging the product into your skin using circular upwards motions. Use daily for sun exposure. Suspend use if irritation occurs

STORAGE AND HANDLING

Protect this product from excessive heat and direct sun

OTHER SAFETY INFORMATION

TRUST MD SPF 30 With Zinc Oxide STEM CELL FACE CREAM

SPF 30

Vitamins B, C, E

Plant-Based Stem Cells

1.7 fl.oz (50mL)

Drug Facts

Active Ingredients-------------------- Purpose

Zinc Oxide 15.84%-----------Sunscreen

Uses

Help prevent sunburn If used as directed with other sun protection measures(see Directions), decreases the risk of skin cancer and early skin aging caused by the sun.

Warnings

For external use only

Do not use on damaged or broken skin

When using this product, keep out of eyes. Rinse with water to remove

Stop using and ask a doctor if a rash occurs

Keep out of reach of children. In case of ingestion, get medical help or contact a Poison Control Center right away.

Directions

Apply product to the face and neck by gently massaging the product into your skin using circular upwards motions. Use daily for sun exposure. Suspend use if irritation occurs.

Inactive ingredients

Water, Glycerin, Cyclopentasiloxane, Cetyl PEG/PPG-10/1 Dimethicone, Aloe Barbadensis Leaf Water, Cocos Nucifera (Coconut) Oil, Butyrospermum Parkii (Shea) Butter, Ricinus Communis (Castor) Seed Oil, Polyglyceryl-3 Diisostearate, Helianthus Annuus (Sunflower) Seed Oil, Sodium Chloride, Ethylhexyl Palmitate, Caprylic/Capric Triglyceride, Dimethicone Crosspolymer, Sodium Hyaluronate, Ascorbic Acid, Tocopheryl Acetate, Panthenol, 1,2-Hexanediol, Hydroxyacetophenone, Butylene Glycol, Dimethicone, Triethoxycaprylylsilane, Fragrance, Disodium EDTA, Malus Domestica Fruit Cell Culture Extract, Phenoxyethanol, Glycyrrhiza Glabra (Licorice) Root Extract, Centella Asiatica Extract, Xanthan Gum, Scutellaria Baicalensis Root Extract, Polygonum Cuspidatum Root Extract, Chamomilla Recutita (Matricaria) Flower Extract, Camellia Sinensis Leaf Extract, Rosmarinus Officinalis (Rosemary) Leaf Extract, Lecithin.

Other information

Protect this product from excessive heat and direct sun

Questions or comments?

hello@trustmd.com

PLANT-BASED STEM CELLS:

Improves texture, fine lines, and skin tone by

restoring cells natural balance and pH.

Promotes collagen production.

HYALURONIC ACID:

Moisturizes individual skin cells, which plumps

and firms the skin for a younger look. lt

repairs and protects youthful skin cells.

VITAMINS B5,C,E:

B5 binds moisture to skin cells, which firms &

plumps the skin, and erases fine lines

C improves skin tone and promotes collagen

production for overall glow.

E nourishes the lipid barrier to stop moisture

evaporation, so results keep building with

continued use!

From real women who trust science!

@TrustMDskin

Distributed by

TRUST MD

9830 Norwalk Blvd, Santa Fe

Springs CA 90670

Made in P.R.C

hello@trustmd.com

www.TrustMD.com

SKU#MD-27-FC

INDICATIONS AND USAGE

Help prevent sunburn If used as directed with other sun protection measures(see Directions)

RECENT MAJOR CHANGES

Indications and Usage

Update to more accurate description

INACTIVE INGREDIENT

Water, Glycerin, Ethylhexyl Palmitate, Caprylic/Capric Triglyceride, Cyclopentasiloxane, Cetyl PEG/PPG-10/1 Dimethicone, Polyglyceryl-3 Diisostearate, Helianthus Annuus (Sunflower) Seed Oil, Sodium Chloride, Dimethicone Crosspolymer, Tocopheryl Acetate, Panthenol, 1,2-Hexanediol, Hydroxyacetophenone, Butylene Glycol, Aloe Barbadensis Leaf Water, Dimethicone, Triethoxycaprylylsilane, Cocos Nucifera (Coconut) Oil, Butyrospermum Parkii (Shea) Butter, Ricinus Communis (Castor) Seed Oil, Ascorbic Acid, Fragrance, Disodium EDTA, Sodium Hyaluronate, Malus Domestica Fruit Cell Culture Extract, Phenoxyethanol, Glycyrrhiza Glabra (Licorice) Root Extract, Centella Asiatica Extract, Xanthan Gum, Scutellaria Baicalensis Root Extract, Polygonum Cuspidatum Root Extract, Chamomilla Recutita (Matricaria) Flower Extract, Camellia Sinensis Leaf Extract, Rosmarinus Officinalis (Rosemary) Leaf Extract, Lecithin